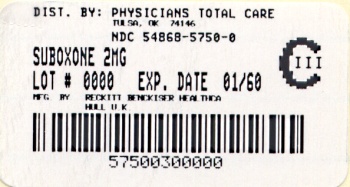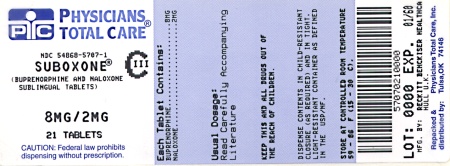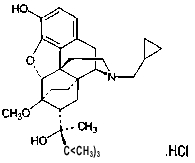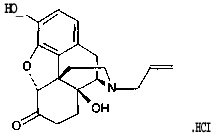 DRUG LABEL: Suboxone
NDC: 54868-5750 | Form: TABLET
Manufacturer: Physicians Total Care, Inc.
Category: prescription | Type: HUMAN PRESCRIPTION DRUG LABEL
Date: 20100727
DEA Schedule: CIII

ACTIVE INGREDIENTS: BUPRENORPHINE HYDROCHLORIDE 2 mg/1 1; NALOXONE HYDROCHLORIDE 0.5 mg/1 1
INACTIVE INGREDIENTS: LACTOSE; MANNITOL; STARCH, CORN; POVIDONE K30; CITRIC ACID MONOHYDRATE; SODIUM CITRATE; FD&C YELLOW NO. 6; MAGNESIUM STEARATE

Rx only

Under the Drug Addiction Treatment Act of 2000 (DATA) codified at 21 U.S.C. 823(g), prescription use of this product in the treatment of opioid dependence is limited to physicians who meet certain qualifying requirements, and have notified the Secretary of Health and Human Services (HHS) of their intent to prescribe this product for the treatment of opioid dependence.

DESCRIPTION

SUBOXONE sublingual tablets contain buprenorphine HCl and naloxone HCl dihydrate at a ratio of 4:1 buprenorphine: naloxone (ratio of free bases).

SUBUTEX sublingual tablets contain buprenorphine HCl.

Buprenorphine is a partial agonist at the mu-opioid receptor and an antagonist at the kappa-opioid receptor. Naloxone is an antagonist at the mu-opioid receptor.

Buprenorphine is a Schedule III narcotic under the Controlled Substances Act.

Buprenorphine hydrochloride is a white powder, weakly acidic with limited solubility in water (17mg/mL). Chemically, buprenorphine is 17-(cyclopropylmethyl)-α-(1,1-dimethylethyl)-4,5-epoxy-18,19-dihydro-3-hydroxy-6-methoxy- α-methyl-6,14-ethenomorphinan-7-methanol, hydrochloride [5α, 7α(S)]-. Buprenorphine hydrochloride has the molecular formula C29 H41N04 HCl and the molecular weight is 504.10.

STRUCTURAL FORMULA OF BUPRENORPHINE

Naloxone hydrochloride is a white to slightly off-white powder and is soluble in water, in dilute acids and in strong alkali. Chemically, naloxone is 17-Allyl-4,5 α -epoxy-3,14-dihydroxymorphinan-6-one hydrochloride. Naloxone Hydrochloride has the molecular formula C19 H21 N04 HCl .2H2 0 and the molecular weight is 399.87.

STRUCTURAL FORMULA OF NALOXONE

SUBOXONE is an uncoated hexagonal orange tablet intended for sublingual administration. It is available in two dosage strengths, 2mg buprenorphine with 0.5mg naloxone, and 8mg buprenorphine with 2mg naloxone free bases. Each tablet also contains lactose, mannitol, cornstarch, povidone K30, citric acid, sodium citrate, FD&C Yellow No.6 color, magnesium stearate, and the tablets also contain Acesulfame K sweetener and a lemon / lime flavor.

SUBUTEX is an uncoated oval white tablet intended for sublingual administration. It is available in two dosage strengths, 2mg buprenorphine and 8mg buprenorphine free base. Each tablet also contains lactose, mannitol, cornstarch, povidone K30, citric acid, sodium citrate and magnesium stearate.

CLINICAL PHARMACOLOGY

Enter section text here

Subjective Effects:

Comparisons of buprenorphine with full agonists such as methadone and hydromorphone suggest that sublingual buprenorphine produces typical opioid agonist effects which are limited by a ceiling effect.

In non-dependent subjects, acute sublingual doses of SUBOXONE tablets produced opioid agonist effects, which reached a maximum between doses of 8 mg and 16mg of SUBUTEX. The effects of 16mg SUBOXONE were similar to those produced by 16mg SUBUTEX (buprenorphine alone).

Opioid agonist ceiling effects were also observed in a double-blind, parallel group, dose ranging comparison of single doses of buprenorphine sublingual solution (1, 2, 4, 8, 16, or 32 mg), placebo, and a full agonist control at various doses. The treatments were given in ascending dose order at intervals of at least one week to 16 opioid-experienced, non-dependent subjects. Both drugs produced typical opioid agonist effects. For all the measures for which the drugs produced an effect, buprenorphine produced a dose-related response but, in each case, there was a dose that produced no further effect. In contrast, the highest dose of the full agonist control always produced the greatest effects. Agonist objective rating scores remained elevated for the higher doses of buprenorphine (8-32 mg) longer than for the lower doses and did not return to baseline until 48 hours after drug administrations. The onset of effects appeared more rapidly with buprenorphine than with the full agonist control, with most doses nearing peak effect after 100 minutes for buprenorphine compared to 150 minutes for the full agonist control.

Physiologic Effects:

Buprenorphine in intravenous (2mg, 4mg, 8mg, 12mg and 16 mg) and sublingual (12mg) doses has been administered to non-dependent subjects to examine cardiovascular, respiratory and subjective effects at doses comparable to those used for treatment of opioid dependence. Compared with placebo, there were no statistically significant differences among any of the treatment conditions for blood pressure, heart rate, respiratory rate, O2 saturation or skin temperature across time. Systolic BP was higher in the 8 mg group than placebo (3 hour AUC values). Minimum and maximum effects were similar across all treatments. Subjects remained responsive to low voice and responded to computer prompts. Some subjects showed irritability, but no other changes were observed.

The respiratory effects of sublingual buprenorphine were compared with the effects of methadone in a double-blind, parallel group, dose ranging comparison of single doses of buprenorphine sublingual solution (1, 2, 4, 8, 16, or 32 mg) and oral methadone (15, 30, 45, or 60 mg) in non-dependent, opioid-experienced volunteers. In this study, hypoventilation not requiring medical intervention was reported more frequently after buprenorphine doses of 4 mg and higher than after methadone. Both drugs decreased O2 saturation to the same degree.

Effect of Naloxone:

Physiologic and subjective effects following acute sublingual administration of SUBOXONE and SUBUTEX tablets were similar at equivalent dose levels of buprenorphine. Naloxone, in the SUBOXONE formulation, had no clinically significant effect when administered by the sublingual route, although blood levels of the drug were measurable. SUBOXONE, when administered sublingually even to an opioid-dependent population, was recognized as an opioid agonist, whereas when administered intramuscularly, combinations of buprenorphine with naloxone produced opioid antagonist actions similar to naloxone. In methadone-maintained patients and heroin-dependent subjects, intravenous administration of buprenorphine/naloxone combinations precipitated opioid withdrawal and was perceived as unpleasant and dysphoric. In morphine-stabilized subjects, intravenously administered combinations of buprenorphine with naloxone produced opioid antagonist and withdrawal effects that were ratio-dependent; the most intense withdrawal effects were produced by 2:1 and 4:1 ratios, less intense by an 8:1 ratio. SUBOXONE tablets contain buprenorphine with naloxone at a ratio of 4:1.

Pharmacokinetics:

Absorption:

Plasma levels of buprenorphine increased with the sublingual dose of SUBUTEX and SUBOXONE, and plasma levels of naloxone increased with the sublingual dose of SUBOXONE (Table 1). There was a wide inter-patient variability in the sublingual absorption of buprenorphine and naloxone, but within subjects the variability was low. Both Cmax and AUC of buprenorphine increased in a linear fashion with the increase in dose (in the range of 4 to 16 mg), although the increase was not directly dose-proportional.

Naloxone did not affect the pharmacokinetics of buprenorphine and both SUBUTEX and SUBOXONE deliver similar plasma concentrations of buprenorphine. The levels of naloxone were too low to assess dose-proportionality. At the three naloxone doses of 1 mg, 2 mg, and 4 mg, levels above the limit of quantitation (0.05 ng/mL) were not detected beyond 2 hours in seven of eight subjects. In one individual, at the 4mg dose, the last measurable concentration was at 8 hours. Within each subject (for most of the subjects), across the doses there was a trend toward an increase in naloxone concentrations with increase in dose. Mean peak naloxone levels ranged from 0.11 to 0.28ng/mL in the dsose range of 1-4 mg.

Table 1. Pharmacokinetic parameters of buprenorphine after the administration of 4 mg, 8mg, and 16 mg Suboxone® doses and 16mg Subutex® dose (mean (%CV)).
Pharmacokinetic Parameter | Suboxone® 4 mg | Suboxone® 8 mg | Suboxone® 16 mg | Subutex® 16 mg
Cmax, ng/mL | 1.84(39) | 3.0(51) | 5.95(38) | 5.47(23)
AUC0-48, hour. ng/mL | 12.52(35) | 20.22 (43) | 34.89 (33) | 32.63 (25)

Distribution:

Buprenorphine is approximately 96% protein bound, primarily to alpha and beta globulin.

Naloxone is approximately 45% protein bound, primarily to albumin.

Metabolism:

Buprenorphine undergoes both N-dealkylation to norbuprenorphine and glucuronidation. The N-dealkylation pathway is mediated by cytochrome P-450 3A4 isozyme. Norbuprenorphine, an active metabolite, can further undergo glucuronidation.

Naloxone undergoes direct glucuronidation to naloxone 3-glucuronide as well as N-dealkylation, and reduction of the 6-oxo group.

Elimination:

A mass balance study of buprenorphine showed complete recovery of radiolabel in urine (30%) and feces (69%) collected up to 11 days after dosing. Almost all of the dose was accounted for in terms of buprenorphine, norbuprenorphine, and two unidentified buprenorphine metabolites. In urine, most of buprenorphine and norbuprenorphine was conjugated (buprenorphine, 1% free and 9.4% conjugated; norbuprenorphine, 2.7% free and 11% conjugated). In feces, almost all of the buprenorphine and norbuprenorphine were free (buprenorphine, 33% free and 5% conjugated; norbuprenorphine, 21% free and 2% conjugated).

Buprenorphine has a mean elimination half-life from plasma of 37 h.

Naloxone has a mean elimination half-life from plasma of 1.1 h.

Special Populations:

Hepatic Disease:

The effect of hepatic impairment on the pharmacokinetics of buprenorphine and naloxone is unknown. Since both drugs are extensively metabolized, the plasma levels will be expected to be higher in patients with moderate and severe hepatic impairment. However, it is not known whether both drugs are affected to the same degree. Therefore, in patients with hepatic impairment dosage should be adjusted and patients should be observed for symptoms of precipitated opioid withdrawal.

Renal Disease:

No differences in buprenorphine pharmacokinetics were observed between 9 dialysis-dependent and 6 normal patients following intravenous administration of 0.3mg buprenorphine.

The effects of renal failure on naloxone pharmacokinetics are unknown.

Drug-drug interactions:

CYP3A4 Inhibitors and Inducers: A pharmacokinetic interaction study of ketoconazole (400 mg/day), a potent inhibitor of CYP 3A4, in 12 patients stabilized on SUBOXONE [8mg (n=1) or 12mg (n=5) or 16mg (n=6)] resulted in increases in buprenorphine mean Cmax values (from 4.3 to 9.8, 6.3 to 14.4 and 9.0 to 17.1) and mean AUC values (from 30.9 to 46.9, 41.9 to 83.2 and 52.3 to 120) respectively. Subjects receiving SUBUTEX or SUBOXONE should be closely monitored and may require dose-reduction if inhibitors of CYP 3A4 such as azole antifungal agents (e.g. ketoconazole), macrolide antibiotics (e.g., erythromycin) and HIV protease inhibitors (e.g. ritonavir, indinavir and saquinavir) are co-administered. The interaction of buprenorphine with CYP 3A4 inducers has not been investigated; therefore it is recommended that patients receiving SUBUTEX or SUBOXONE should be closely monitored if inducers of CYP 3A4 (e.g. phenobarbital, carbamazepine, phenytoin, rifampicin) are co-administered (SEE WARNINGS).

CLINICAL STUDIES

Clinical data on the safety and efficacy of SUBOXONE and SUBUTEX are derived from studies of buprenorphine sublingual tablet formulations, with and without naloxone, and from studies of sublingual administration of a more bioavailable ethanolic solution of buprenorphine.

SUBOXONE tablets have been studied in 575 patients, SUBUTEX tablets in 1834 patients and buprenorphine sublingual solutions in 2470 patients. A total of 1270 females have received buprenorphine in clinical trials. Dosing recommendations are based on data from one trial of both tablet formulations and two trials of the ethanolic solution. All trials used buprenorphine in conjunction with psychosocial counseling as part of a comprehensive addiction treatment program. There have been no clinical studies conducted to assess the efficacy of buprenorphine as the only component of treatment.

In a double blind placebo- and active controlled study, 326 heroin-addicted subjects were randomly assigned to either SUBOXONE 16 mg per day, 16 mg SUBUTEX per day or placebo tablets. For subjects randomized to either active treatment, dosing began with one 8 mg tablet of SUBUTEX on Day 1, followed by 16 mg (two 8 mg tablets) of SUBUTEX on Day 2. On Day 3, those randomized to receive SUBOXONE were switched to the combination tablet. Subjects randomized to placebo received one placebo tablet on Day 1 and two placebo tablets per day thereafter for four weeks. Subjects were seen daily in the clinic (Monday through Friday) for dosing and efficacy assessments. Take-home doses were provided for weekends. Subjects were instructed to hold the medication under the tongue for approximately 5 to 10 minutes until completely dissolved. Subjects received one hour of individual counseling per week and a single session of HIV education. The primary study comparison was to assess the efficacy of SUBUTEX and SUBOXONE individually against placebo. The percentage of thrice-weekly urine samples that were negative for non-study opioids was statistically higher for both SUBUTEX and SUBOXONE, than for placebo.

In a double-blind, double-dummy, parallel-group study comparing buprenorphine ethanolic solution to a full agonist active control, 162 subjects were randomized to receive the ethanolic sublingual solution of buprenorphine at 8 mg/day (a dose which is roughly comparable to a dose of 12 mg/day of SUBUTEX or SUBOXONE), or two relatively low doses of active control, one of which was low enough to serve as an alternative to placebo, during a 3-10 day induction phase, a 16-week maintenance phase and a 7-week detoxification phase. Buprenorphine was titrated to maintenance dose by Day 3; active control doses were titrated more gradually.

Maintenance dosing continued through Week 17, and then medications were tapered by approximately 20-30% per week over Weeks 18-24, with placebo dosing for the last two weeks. Subjects received individual and/or group counseling weekly.

Based on retention in treatment and the percentage of thrice-weekly urine samples negative for non-study opioids, buprenorphine was more effective than the low dose of the control, in keeping heroin addicts in treatment and in reducing their use of opioids while in treatment. The effectiveness of buprenorphine, 8 mg per day was similar to that of the moderate active control dose, but equivalence was not demonstrated.

In a dose-controlled, double-blind, parallel-group, 16-week study, 731 subjects were randomized to receive one of four doses of buprenorphine ethanolic solution. Buprenorphine was titrated to maintenance doses over 1-4 days (Table 2) and continued for 16 weeks. Subjects received at least one session of AIDS education and additional counseling ranging from one hour per month to one hour per week, depending on site.

Table 2. Doses of Sublingual Buprenorphine Solution used for Induction in a Double-Blind Dose Ranging Study
Target dose of Buprenorphine* | Induction Dose | Maintenance dose
Day 1 | Day 2 | Day 3
1 mg | 1 mg | 1 mg | 1 mg | 1 mg
4 mg | 2 mg | 4 mg | 4 mg | 4 mg
8 mg | 2 mg | 4 mg | 8 mg | 8 mg
16 mg | 2 mg | 4 mg | 8 mg | 16 mg

* Sublingual solution. Doses in this tabe cannot necessarily be delivered in tablet form, but for comparison purposes:

2 mg solution would be roughly equivalent to 3 mg tablet

4 mg solution would be roughly equivalent to 6 mg tablet

8 mg solution would be roughly equivalent to 12 mg tablet

16 mg solution would be roughly equivalent to 24 mg tablet

Based on retention in treatment and the percentage of thrice-weekly urine samples negative for non-study opioids, the three highest tested doses were superior to the 1 mg dose. Therefore, this study showed that a range of buprenorphine doses may be effective. The 1 mg dose of buprenorphine sublingual solution can be considered to be somewhat lower than a 2 mg tablet dose. The other doses used in the study encompass a range of tablet doses from approximately 6 mg to approximately 24 mg.

INDICATIONS AND USAGE

SUBOXONE and SUBUTEX are indicated for the treatment of opioid dependence.

CONTRAINDICATIONS

SUBOXONE and SUBUTEX should not be administered to patients who have been shown to be hypersensitive to buprenorphine, and SUBOXONE should not be administered to patients who have been shown to be hypersensitive to naloxone.

WARNINGS

Enter section text here

Respiratory Depression:

Significant respiratory depression has been associated with buprenorphine, particularly by the intravenous route. A number of deaths have occurred when addicts have intravenously misused buprenorphine, usually with benzodiazepines concomitantly. Deaths have also been reported in association with concomitant administration of buprenorphine with other depressants such as alcohol or other opioids. Patients should be warned of the potential danger of the self-administration of benzodiazepines or other depressants while under treatment with SUBUTEX or SUBOXONE.

IN THE CASE OF OVERDOSE, THE PRIMARY MANAGEMENT SHOULD BE THE RE-ESTABLISHMENT OF ADEQUATE VENTILATION WITH MECHANICAL ASSISTANCE OF RESPIRATION, IF REQUIRED. NALOXONE MAY NOT BE EFFECTIVE IN REVERSING ANY RESPIRATORY DEPRESSION PRODUCED BY BUPRENORPHINE.

SUBOXONE and SUBUTEX should be used with caution in patients with compromised respiratory function (e.g., chronic obstructive pulmonary disease, cor pulmonale, decreased respiratory reserve, hypoxia, hypercapnia, or pre-existing respiratory depression).

CNS Depression:

Patients receiving buprenorphine in the presence of other narcotic analgesics, general anesthetics, benzodiazepines, phenothiazines, other tranquilizers, sedative/hypnotics or other CNS depressants (including alcohol) may exhibit increased CNS depression. When such combined therapy is contemplated, reduction of the dose of one or both agents should be considered.

Dependence:

Buprenorphine is a partial agonist at the mu-opiate receptor and chronic administration produces dependence of the opioid type, characterized by withdrawal upon abrupt discontinuation or rapid taper. The withdrawal syndrome is milder than seen with full agonists, and may be delayed in onset.

Hepatitis, hepatic events:

Cases of cytolytic hepatitis and hepatitis with jaundice have been observed in the addict population receiving buprenorphine both in clinical trials and in post-marketing adverse event reports. The spectrum of abnormalities ranges from transient asymptomatic elevations in hepatic transaminases to case reports of hepatic failure, hepatic necrosis, hepatorenal syndrome, and hepatic encephalopathy. In many cases, the presence of preexisting liver enzyme abnormalities, infection with hepatitis B or hepatitis C virus, concomitant usage of other potentially hepatotoxic drugs, and ongoing injecting drug use may have played a causative or contributory role. In other cases, insufficient data were available to determine the etiology of the abnormality. The possibility exists that buprenorphine had a causative or contributory role in the development of the hepatic abnormality in some cases. Measurements of liver function tests prior to initiation of treatment is recommended to establish a baseline. Periodic monitoring of liver function tests during treatment is also recommended. A biological and etiological evaluation is recommended when a hepatic event is suspected. Depending on the case, the drug should be carefully discontinued to prevent withdrawal symptoms and a return to illicit drug use, and strict monitoring of the patient should be initiated.

Allergic Reactions:

Cases of acute and chronic hypersensitivity to buprenorphine have been reported both in clinical trials and in the post-marketing experience. The most common signs and symptoms include rashes, hives, and pruritus. Cases of bronchospasm, angioneurotic edema, and anaphylactic shock have been reported. A history of hypersensitivity to buprenorphine is a contraindication to Subutex or Suboxone use. A history of hypersensitivity to naloxone is a contraindication to Suboxone use.

Use in Ambulatory Patients:

SUBOXONE and SUBUTEX may impair the mental or physical abilities required for the performance of potentially dangerous tasks such as driving a car or operating machinery, especially during drug induction and dose adjustment. Patients should be cautioned about operating hazardous machinery, including automobiles, until they are reasonably certain that buprenorphine therapy does not adversely affect their ability to engage in such activities. Like other opioids, SUBOXONE and SUBUTEX may produce orthostatic hypotension in ambulatory patients.

Head Injury and Increased Intracranial Pressure:

SUBOXONE and SUBUTEX, like other potent opioids, may elevate cerebrospinal fluid pressure and should be used with caution in patients with head injury, intracranial lesions and other circumstances where cerebrospinal pressure may be increased. SUBOXONE and SUBUTEX can produce miosis and changes in the level of consciousness that may interfere with patient evaluation.

Opioid withdrawal effects:

Because it contains naloxone, SUBOXONE is highly likely to produce marked and intense withdrawal symptoms if misused parenterally by individuals dependent on opioid agonists such as heroin, morphine, or methadone. Sublingually, SUBOXONE may cause opioid withdrawal symptoms in such persons if administered before the agonist effects of the opioid have subsided.

PRECAUTIONS

Enter section text here

General:

SUBOXONE and SUBUTEX should be administered with caution in elderly or debilitated patients and those with severe impairment of hepatic, pulmonary, or renal function; myxedema or hypothyroidism, adrenal cortical insufficiency (e.g., Addison's disease); CNS depression or coma; toxic psychoses; prostatic hypertrophy or urethral stricture; acute alcoholism; delirium tremens; or kyphoscoliosis.

The effect of hepatic impairment on the pharmacokinetics of buprenorphine and naloxone is unknown. Since both drugs are extensively metabolized, the plasma levels will be expected to be higher in patients with moderate and severe hepatic impairment. However, it is not known whether both drugs are affected to the same degree. Therefore, dosage should be adjusted and patients should be watched for symptoms of precipitated opioid withdrawal.

Buprenorphine has been shown to increase intracholedochal pressure, as do other opioids, and thus should be administered with caution to patients with dysfunction of the biliary tract.

As with other mu-opioid receptor agonists, the administration of SUBOXONE or SUBUTEX may obscure the diagnosis or clinical course of patients with acute abdominal conditions.

Drug Interactions:

Buprenorphine is metabolized to norbuprenorphine by cytochrome CYP 3A4. Because CYP 3A4 inhibitors may increase plasma concentrations of buprenorphine, patients already on CYP 3A4 inhibitors such as azole antifungals (e.g. ketoconazole), macrolide antibiotics (e.g. erythromycin), and HIV protease inhibitors (e.g. ritonavir, indinavir and saquinavir) should have their dose of SUBUTEX or SUBOXONE adjusted.

Based on anecdotal reports, there may be an interaction between buprenorphine and benzodiazepines. There have been a number of reports in the post-marketing experience of coma and death associated with the concomitant intravenous misuse of buprenorphine and benzodiazepines by addicts. In many of these cases, buprenorphine was misused by self-injection of crushed SUBUTEX tablets. SUBUTEX and SUBOXONE should be prescribed with caution to patients on benzodiazepines or other drugs that act on the central nervous system, regardless of whether these drugs are taken on the advice of a physician or are taken as drugs of abuse. Patients should be warned of the potential danger of the intravenous self-administration of benzodiazepines while under treatment with SUBOXONE or SUBUTEX.

Information for Patients:

Patients should inform their family members that, in the event of emergency, the treating physician or emergency room staff should be informed that the patient is physically dependent on narcotics and that the patient is being treated with SUBOXONE or SUBUTEX.

Patients should be cautioned that a serious overdose and death may occur if benzodiazepines, sedatives, tranquilizers, antidepressants, or alcohol are taken at the same time as SUBOXONE or SUBUTEX.

SUBOXONE and SUBUTEX may impair the mental or physical abilities required for the performance of potentially dangerous tasks such as driving a car or operating machinery, especially during drug induction and dose adjustment. Patients should be cautioned about operating hazardous machinery, including automobiles, until they are reasonably certain that buprenorphine therapy does not adversely affect their ability to engage in such activities. Like other opioids, SUBOXONE and SUBUTEX may produce orthostatic hypotension in ambulatory patients.

Patients should consult their physician if other prescription medications are currently being used or are prescribed for future use.

Carcinogenesis, Mutagenesis and Impairment of Fertility:

Carcinogenicity: Carcinogenicity data on SUBOXONE are not available. Carcinogenicity studies of buprenorphine were conducted in Sprague-Dawley rats and CD-1 mice. Buprenorphine was administered in the diet to rats at doses of 0.6, 5.5, and 56 mg/kg/day (estimated exposure was approximately 0.4, 3 and 35 times the recommended human daily sublingual dose of 16 mg on a mg/m^2 basis) for 27 months. Statistically significant dose-related increases in testicular interstitial (Leydig's) cell tumors occurred, according to the trend test adjusted for survival. Pair-wise comparison of the high dose against control failed to show statistical significance. In an 86-week study in CD-1 mice, buprenorphine was not carcinogenic at dietary doses up to 100 mg/kg/day (estimated exposure was approximately 30 times the recommended human daily sublingual dose of 16 mg on a mg/m^2 basis).

Mutagenicity:

SUBOXONE: The 4:1 combination of buprenorphine and naloxone was not mutagenic in a bacterial mutation assay (Ames test) using four strains of S. typhimurium and two strains of E coli. The combination was not clastogenic in an in vitro cytogenetic assay in human lymphocytes, or in an intravenous micronucleus test in the rat.

SUBUTEX: Buprenorphine was studied in a series of tests utilizing gene, chromosome, and DNA interactions in both prokaryotic and eukaryotic systems. Results were negative in yeast (Saccharomyces cerevisiae) for recombinant, gene convertant, or forward mutations; negative in Bacillus subtilis "rec"assay, negative for clastogenicity in CHO cells, Chinese hamster bone marrow and spermatogonia cells, and negative in the mouse lymphoma L5178Y assay. Results were equivocal in the Ames test: negative in studies in two laboratories, but positive for frame shift mutation at a high dose (5mg/plate) in a third study. Results were positive in the Green-Tweets (E. coli) survival test, positive in a DNA synthesis inhibition (DSI) test with testicular tissue from mice, for both in vivo and in vitro incorporation of [^3H]thymidine, and positive in unscheduled DNA synthesis (UDS) test using testicular cells from mice.

Impairment of Fertility:

SUBOXONE: Dietary administration of SUBOXONE in the rat at dose levels of 500 ppm or greater (equivalent to approximately 4/mg/kg/day or greater; estimated exposure was approximately 28 times the recommended human daily sublingual dose of 16 mg on a mg/m^2 basis) produced a reduction in fertility demonstrated by reduced female conception rates. A dietary dose of 100 ppm (equivalent to approximately 10 mg/kg/day; estimated exposure was approximately 6 times the recommended human daily sublingual dose of 16 mg on a mg/m^2 basis) had no adverse effect on fertility.

SUBUTEX: Reproduction studies of buprenorphine in rats demonstrated no evidence of impaired fertility at daily oral doses up to 80mg/kg/day (estimated exposure was approximately 50 times the recommended human daily sublingual dose of 16 mg on a mg/m^2 basis) or up to 5mg/kg/day im or sc (estimated exposure was approximately 3 times the recommended human daily sublingual dose of 16 mg on a mg/m^2 basis).

Pregnancy:

Pregnancy Category C: Teratogenic effects:

SUBOXONE: Effects on embryo-fetal development were studied in Sprague-Dawley rats and Russian white rabbits following oral (1:1) and intramuscular (3:2) administration of mixtures of buprenorphine and naloxone. Following oral administration to rats and rabbits, no teratogenic effects were observed at doses up to 250 mg/kg/day and 40 mg/kg/day, respectively (estimated exposure was approximately 150 times and 50 times, respectively, the recommended human daily sublingual dose of 16 mg on a mg/m^2 basis). No definitive drug-related teratogenic effects were observed in rats and rabbits at intramuscular doses up to 30 mg/kg/day (estimated exposure was approximately 20 times and 35 times, respectively, the recommended human daily dose of 16 mg on a mg/m^2 basis). Acephalus was observed in one rabbit fetus from the low-dose group and omphacele was observed in two rabbit fetuses from the same litter in the mid-dose group; no findings were observed in fetuses from the high-dose group. Following oral administration to the rat, dose-related post-implantation losses, evidenced by increases in the numbers of early resorptions with consequent reductions in the numbers of fetuses, were observed at doses of 10 mg/kg/day or greater (estimated exposure was approximately 6 times the recommended human daily sublingual dose of 16 mg on a mg/m^2 basis). In the rabbit, increased post-implantation losses occurred at an oral dose of 40 mg/kg/day. Following intramuscular administration in the rat and the rabbit, post-implantation losses, as evidenced by decreases in live fetuses and increases in resorptions, occurred at 30 mg/kg/day.

SUBUTEX: Buprenorphine was not teratogenic in rats or rabbits after im or sc doses up to 5 mg/kg/day (estimated exposure was approximately 3 and 6 times, respectively, the recommended human daily sublingual dose of 16 mg on a mg/m^2 basis), after iv doses up to 0.8 mg/kg/day (estimated exposure was approximately 0.5 times and equal to, respectively, the recommended human daily sublingual dose of 16 mg on a mg/m^2 basis), or after oral doses up to 160 mg/kg/day in rats (estimated exposure was approximately 95 times the recommended human daily sublingual dose of 16 mg on a mg/m^2 basis) and 25 mg/kg/day in rabbits (estimated exposure was approximately 30 times the recommended human daily sublingual dose of 16 mg on a mg/m^2 basis). Significant increases in skeletal abnormalities (e.g., extra thoracic vertebra or thoraco-lumbar ribs) were noted in rats after sc administration of 1 mg/kg/day and up (estimated exposure was approximately 0.6 times the recommended human daily sublingual dose of 16 mg on a mg/m^2 basis), but were not observed at oral doses up to 160 mg/kg/day. Increases in skeletal abnormalities in rabbits after im administration of 5 mg/kg/day (estimated exposure was approximately 6 times the recommended human daily sublingual dose of 16 mg on a mg/m^2 basis) or oral administration of 1 mg/kg/day or greater (estimated exposure was approximately equal to the recommended human daily sublingual dose of 16 mg on a mg/m^2 basis) were not statistically significant.

In rabbits, buprenorphine produced statistically significant pre-implantation losses at oral doses of 1 mg/kg/day or greater and post-implantation losses that were statistically significant at iv doses of 0.2 mg/kg/day or greater (estimated exposure was approximately 0.3 times the recommended human daily sublingual dose of 16 mg on a mg/m^2 basis).

There are no adequate and well-controlled studies of SUBOXONE or SUBUTEX in pregnant women. SUBOXONE or SUBUTEX should only be used during pregnancy if the potential benefit justifies the potential risk to the fetus.

Non-teratogenic effects.

Dystocia was noted in pregnant rats treated im with buprenorphine 5 mg/kg/day (approximately 3 times the recommended human daily sublingual dose of 16 mg on a mg/m^2 basis). Both fertility and peri- and postnatal development studies with buprenorphine in rats indicated increases in neonatal mortality after oral doses of 0.8 mg/kg/day and up (approximately 0.5 times the recommended human daily sublingual dose of 16 mg on a mg/m^2 basis), after im doses of 0.5 mg/kg/day and up (approximately 0.3 times the recommended human daily sublingual dose of 16 mg on a mg/m^2 basis), and after sc doses of 0.1 mg/kg/day and up (approximately 0.06 times the recommended human daily sublingual dose of 16 mg on a mg/m^2 basis). Delays in the occurrence of righting reflex and startle response were noted in rat pups at an oral dose of 80 mg/kg/day (approximately 50 times the recommended human daily sublingual dose of 16 mg on a mg/m^2 basis).

Neonatal Withdrawal:

Neonatal withdrawal has been reported in the infants of women treated with SUBUTEX during pregnancy. From post-marketing reports, the time to onset of neonatal withdrawal symptoms ranged from Day 1 to Day 8 of life with most occurring on Day 1. Adverse events associated with neonatal withdrawal syndrome included hypertonia, neonatal tremor, neonatal agitation, and myoclonus. There have been rare reports of convulsions and in one case, apnea and bradycardia were also reported.

Nursing Mothers:

An apparent lack of milk production during general reproduction studies with buprenorphine in rats caused decreased viability and lactation indices. Use of high doses of sublingual buprenorphine in pregnant women showed that buprenorphine passes into the mother's milk. Breast-feeding is therefore not advised in mothers treated with SUBUTEX or SUBOXONE.

Pediatric Use:

SUBOXONE and SUBUTEX are not recommended for use in pediatric patients. The safety and effectiveness of SUBOXONE and SUBUTEX in patients below the age of 16 have not been established.

ADVERSE REACTIONS

The safety of SUBOXONE has been evaluated in 497 opioid-dependent subjects. The prospective evaluation of SUBOXONE was supported by clinical trials using SUBUTEX (buprenorphine tablets without naloxone) and other trials using buprenorphine sublingual solutions. In total, safety data are available from 3214 opioid-dependent subjects exposed to buprenorphine at doses in the range used in treatment of opioid addiction.

Few differences in adverse event profile were noted between SUBOXONE and SUBUTEX or buprenorphine administered as a sublingual solution.

In a comparative study, adverse event profiles were similar for subjects treated with 16 mg SUBOXONE or 16mg SUBUTEX. The following adverse events were reported to occur by at least 5% of patients in a 4-week study (Table 3).

Table 3. Adverse Events (≥5%) by Body System and Treatment Group in a 4-week Study
 | N(%) | N(%) | N(%)
Body System / Adverse Event (COSTART Terminology) | SUBOXONE 16mg/day N=107 | SUBUTEX 16mg/day N=103 | Placebo N=107
Body as a Whole
Asthenia | 7 (6.5%) | 5 (4.9%) | 7 (6.5%)
Chills | 8 (7.5%) | 8 (7.8%) | 8 (7.5%)
Headache | 39 (36.4%) | 30(29.1%) | 24 (22.4%)
Infection | 6 (5.6%) | 12(11.7%) | 7 (6.5%)
Pain | 24 (22.4%) | 19(18.4%) | 20(18.7%)
Pain Abdomen | 12(11.2%) | 12(11.7%) | 7 (6.5%)
Pain Back | 4 (3.7%) | 8 (7.8%) | 12(11.2%)
Withdrawal Syndrome | 27 (25.2%) | 19(18.4%) | 40 (37.4%)
Cardiovascular System
Vasodilation | 10(9.3%) | 4 (3.9%) | 7 (6.5%)
Digestive System
Constipation | 13(12.1%) | 8 (7.8%) | 3 (2.8%)
Diarrhea | 4 (3.7%) | 5 (4.9%) | 16(15.0%)
Nausea | 16(15.0%) | 14(13.6%) | 12(11.2%)
Vomiting | 8 (7.5%) | 8 (7.8%) | 5 (4.7%)
Nervous System
Insomnia | 15(14.0%) | 22(21.4%) | 17(15.9%)
Respiratory System
Rhinitis | 5 (4.7%) | 10(9.7%) | 14(13.1%)
Skin And Appendages
Sweating | 15(14.0%) | 13(12.6%) | 11 (10.3%)

The adverse event profile of buprenorphine was also characterized in the dose-controlled study of buprenorphine solution, over a range of doses in four months of treatment. Table 4 shows adverse events reported by at least 5% of subjects in any dose group in the dose-controlled study.

Table 4. Adverse Events (≥ 5%) by Body System and Treatment Group in a 16-week Study
Body System /Adverse Event (COSTART Terminology) | Buprenorphine Dose*
Very Low* (N=184) | Low* (N=180) | Moderate* (N=186) | High* (N=181) | Total* (N=731)
N (%) | N (%) | N (%) | N (%) | N (%)
Body as a Whole
Abscess | 9 (5%) | 2(1%) | 3 (2%) | 2(1%) | 16(2%)
Asthenia | 26(14%) | 28(16%) | 26(14%) | 24(13%) | 104(14%)
Chills | 11 (6%) | 12(7%) | 9 (5%) | 10(6%) | 42 (6%)
Fever | 7 (4%) | 2(1%) | 2(1%) | 10(6%) | 21 (3%)
Flu Syndrome. | 4 (2%) | 13(7%) | 19(10%) | 8 (4%) | 44 (6%)
Headache | 51 (28%) | 62 (34%) | 54 (29%) | 53 (29%) | 220 (30%)
Infection | 32(17%) | 39 (22%) | 38 (20%) | 40 (22%) | 149 (20%)
Injury Accidental | 5 (3%) | 10(6%) | 5 (3%) | 5 (3%) | 25 (3%)
Pain | 47 (26%) | 37(21%) | 49 (26%) | 44 (24%) | 177 (24%)
Pain Back | 18(10%) | 29(16%) | 28(15%) | 27 (15%) | 102(14%)
Withdrawal Syndrome | 45 (24%) | 40 (22%) | 41 (22%) | 36 (20%) | 162(22%)
Digestive System
Constipation | 10(5%) | 23(13%) | 23(12%) | 26(14%) | 82(11%)
Diarrhea | 19(10%) | 8 (4%) | 9 (5%) | 4 (2%) | 40 (5%)
Dyspepsia | 6 (3%) | 10(6%) | 4 (2%) | 4 (2%) | 24 (3%)
Nausea | 12 (7%) | 22(12%) | 23(12%) | 18(10%) | 75(10%)
Vomiting | 8 (4%) | 6 (3%) | 10(5%) | 14 (8%) | 38 (5%)
Nervous System
Anxiety | 22(12%) | 24(13%) | 20(11%) | 25(14%) | 91 (12%)
Depression | 24(13%) | 16(9%) | 25(13%) | 18(10%) | 83(11%)
Dizziness | 4 (2%) | 9 (5%) | 7 (4%) | 11 (6%) | 31 (4%)
Insomnia | 42 (23%) | 50 (28%) | 43 (23%) | 51 (28%) | 186(25%)
Nervousness | 12 (7%) | 11 (6%) | 10(5%) | 13 (7%) | 46 (6%)
Somnolence | 5 (3%) | 13(7%) | 9 (5%) | 11 (6%) | 38 (5%)
Respiratory System
Cough Increase | 5 (3%) | 11 (6%) | 6 (3%) | 4 (2%) | 26 (4%)
Pharyngitis | 6 (3%) | 7 (4%) | 6 (3%) | 9 (5%) | 28 (4%)
Rhinitis | 27(15%) | 16(9%) | 1 5 (8%) | 21 (12%) | 79(11%)
Skin And Appendages
Sweat | 23 (13%) | 21 (12%) | 20(11%) | 23(13%) | 87(12%)
Special Senses
Runny Eyes | 13(7%) | 9 (5%) | 6 (3%) | 6 (3%) | 34 (5%)

*Sublingual solution. Doses in this table cannot necessarily be delivered in tablet form, but for comparison purposes:
"Very low" dose (1 mg solution) would be less than a tablet dose of 2 mg
"Low" dose (4mg solution) approximates a 6 mg tablet dose
"Moderate" dose (8mg solution) approximates a 12 mg tablet dose
"High" dose (16mg solution) approximates a 24 mg tablet dose

DRUG ABUSE AND DEPENDENCE

SUBOXONE and SUBUTEX are controlled as Schedule III narcotics under the Controlled Substances Act.

Buprenorphine is a partial agonist at the mu-opioid receptor and chronic administration produces dependence of the opioid type, characterized by moderate withdrawal upon abrupt discontinuation or rapid taper. The withdrawal syndrome is milder than seen with full agonists, and may be delayed in onset (SEE WARNINGS)

Neonatal withdrawal has been reported in the infants of women treated with SUBUTEX during pregnancy (See PRECAUTIONS)

SUBOXONE contains naloxone and if misused parenterally, is highly likely to produce marked and intense withdrawal symptoms in subjects dependent on other opioid agonists.

OVERDOSAGE

Enter section text here

Manifestations:

Manifestations of acute overdose include pinpoint pupils, sedation, hypotension, respiratory depression and death.

Treatment:

The respiratory and cardiac status of the patient should be monitored carefully. In the event of depression of respiratory or cardiac function, primary attention should be given to the re-establishment of adequate respiratory exchange through provision of a patent airway and institution of assisted or controlled ventilation. Oxygen, intravenous fluids, vasopressors, and other supportive measures should be employed as indicated.

IN THE CASE OF OVERDOSE, THE PRIMARY MANAGEMENT SHOULD BE THE RE-ESTABLISHMENT OF ADEQUATE VENTILATION WlTH MECHANICAL ASSISTANCE OF RESPIRATION IF REQUIRED. NALOXONE MAY NOT BE EFFECTIVE IN REVERSING ANY RESPIRATORY DEPRESSION PRODUCED BY BUPRENORPHINE.

High doses of naloxone hydrochloride. 10-35 mg/70 kg may be of limited value in the management of buprenorphine overdose.. Doxapram (a respiratory stimulant) also has been used.

DOSAGE AND ADMINISTRATION

SUBUTEX or SUBOXONE is administered sublingually as a single daily dose in the range of 12 to 16mg/ day. When taken sublingually, SUBOXONE and SUBUTEX have similar clinical effects and are interchangeable. There are no adequate and well-controlled studies using SUBOXONE as initial medication. SUBUTEX contains no naloxone and is preferred for use during induction. Following induction, SUBOXONE, due to the presence of naloxone, is preferred when clinical use includes unsupervised administration. The use of SUBUTEX for unsupervised administration should be limited to those patients who cannot tolerate SUBOXONE, for example those patients who have been shown to be hypersensitive to naloxone.

Method of administration:

SUBOXONE and SUBUTEX tablets should be placed under the tongue until they are dissolved.

For doses requiring the use of more than two tablets, patients are advised to either place all the tablets at once or alternatively (if they cannot fit in more than two tablets comfortably) place two tablets at a time under the tongue. Either way, the patients should continue to hold the tablets under the tongue until they dissolve; swallowing the tablets reduces the bioavailability of the drug. To ensure consistency in bioavailability, patients should follow the same manner of dosing with continued use of the product.

Induction:

Prior to induction, consideration should be given to the type of opioid dependence (i.e. long- or short-acting opioid), the time since last opioid use, and the degree or level of opioid dependence. To avoid precipitating withdrawal, induction with SUBUTEX should be undertaken when objective and clear signs of withdrawal are evident.

In a one-month study of SUBOXONE tablets induction was conducted with SUBUTEX tablets. Patients received 8mg of SUBUTEX on day 1 and 16mg SUBUTEX on day 2. From day 3 onward, patients received SUBOXONE tablets at the same buprenorphine dose as day 2. Induction in the studies of buprenorphine solution was accomplished over 3-4 days, depending on the target dose. In some studies, gradual induction over several days led to a high rate of drop-out of buprenorphine patients during the induction period. Therefore it is recommended that an adequate maintenance dose, titrated to clinical effectiveness, should be achieved as rapidly as possible to prevent undue opioid withdrawal symptoms.

Patients taking heroin or other short-acting opioids:

At treatment initiation, the dose of SUBUTEX should be administered at least 4 hours after the patient last used opioids or preferably when early signs of opioid withdrawal appear.

Patients on methadone or other long-acting opioids:

There is little controlled experience with the transfer of methadone-maintained patients to buprenorphine. Available evidence suggests that withdrawal symptoms are possible during induction to buprenorphine treatment. Withdrawal appears more likely in patients maintained on higher doses of methadone (>30mg) and when the first buprenorphine dose is administered shortly after the last methadone dose.

Maintenance:

SUBOXONE is the preferred medication for maintenance treatment due to the presence of naloxone in the formulation.

Adjusting the dose until the maintenance dose is achieved:

The recommended target dose of SUBOXONE is 16 mg/day. Clinical studies have shown that 16mg of SUBUTEX or SUBOXONE is a clinically effective dose compared with placebo and indicate that doses as low as 12 mg may be effective in some patients. The dosage of SUBOXONE should be progressively adjusted in increments / decrements of 2mg or 4mg to a level that holds the patient in treatment and suppresses opioid withdrawal effects. This is likely to be in the range of 4mg to 24mg per day depending on the individual.

Reducing dosage and stopping treatment:

The decision to discontinue therapy with SUBOXONE or SUBUTEX after a period of maintenance or brief stabilization should be made as part of a comprehensive treatment plan. Both gradual and abrupt discontinuation have been used, but no controlled trials have been undertaken to determine the best method of dose taper at the end of treatment.

HOW SUPPLIED

SUBOXONE is supplied as sublingual tablets in white HDPE bottles.

Hexagonal orange tablets containing 2mg buprenorphine with 0.5mg naloxone

NDC 54868-5750-0 | 30 tablets per bottle

Hexagonal orange tablets containing 8mg buprenorphine with 2mg naloxone

NDC 54868-5707-4
NDC 54868-5707-2
NDC 54868-5707-1
NDC 54868-5707-3
NDC 54868-5707-0

07 tablets per bottle
14 tablets per bottle
21 tablets per bottle
28 tablets per bottle
30 tablets per bottle

Store at 25°C (77°F), excursions permitted to 15-30°C (59-86°F) [see USP Controlled Room Temperature]

Manufactured by:

Reckitt Benckiser Healthcare (UK) Ltd

Hull, UK, HU8 7DS

Distributed by:

Reckitt Benckiser Pharmaceuticals, Inc.

Richmond, VA 23235

Last revised, June 2005

Relabeling and Repackaging by:
Physicians Total Care, Inc.
Tulsa, OK 74146

PRINCIPAL DISPLAY PANEL

SUBOXONE

2 mg tablets

8 mg tablets